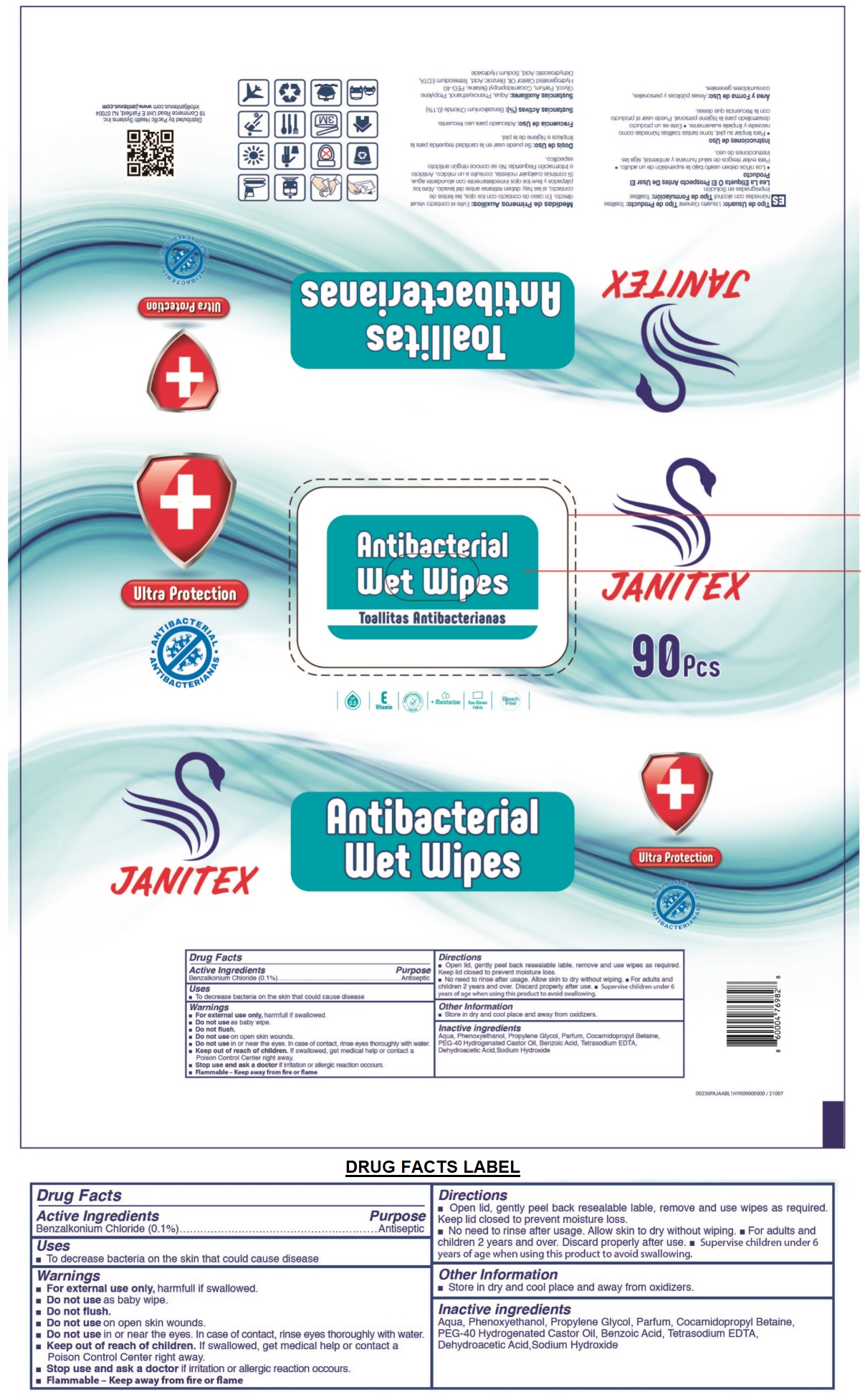 DRUG LABEL: JANITEX ANTIBACTERIAL WET WIPES
NDC: 79519-050 | Form: CLOTH
Manufacturer: Pacific Health Systems Inc.
Category: otc | Type: HUMAN OTC DRUG LABEL
Date: 20200811

ACTIVE INGREDIENTS: BENZALKONIUM CHLORIDE 0.1 g/100 g
INACTIVE INGREDIENTS: WATER; PHENOXYETHANOL; PROPYLENE GLYCOL; COCAMIDOPROPYL BETAINE; POLYOXYL 40 HYDROGENATED CASTOR OIL; BENZOIC ACID; EDETATE SODIUM; DEHYDROACETIC ACID; SODIUM HYDROXIDE

JANITEX Antibacterial Wet Wipes

Active Ingredients

Benzalkonium Chloride (0.1%)

Purpose

Antiseptic

Uses

- To decrease bacteria on the skin that could cause disease

Warnings

- For external use only, harmful if swallowed.
- Do not use as baby wipe.
- Do not flush.
- Do not use on open skin wounds.
- Do not use in or near the eyes. In case of contact, rinse eyes thoroughly with water.
- Stop use and ask a doctor if irritation or allergic reaction occurs.
- Flammable - Keep away from fire or flame

- Keep out of reach of children. If swallowed, get medical help or contact a Poison Control Center right away.

Directions

• Open lid, gently peel back resealable label, remove and use wipes as required. Keep lid closed to prevent moisture loss.

• No need to rinse after usage. Allow skin to dry without wiping. • For adults and children 2 years and over. Discard properly after use. • Supervise children under 6 years of age when using this product to avoid swallowing.

Other Information

- Store in dry and cool place and away from oxidizers.

Inactive ingredients

Aqua, Phenoxyethanol, Propylene Glycol, Parfum, Cocamidopropyl Betaine, PEG-40 Hydrogenated Castor Oil, Benzoic Acid, Tetrasodium EDTA, Dehydroacetic Acid, Sodium Hydroxide

pH 5.5

E Vitamin

DERMATOLOGICALLY TESTED

+ moisturizer

non-woven fabric

Bleach Free

Ultra Protection

ANTIBACTERIAL

Distributed by Pacific Health Systems Inc.

19 Commerce Road Unit E Fairfield, NJ 07004

info@janitexus.com www.janitexus.com